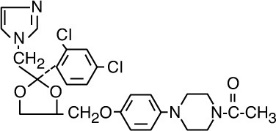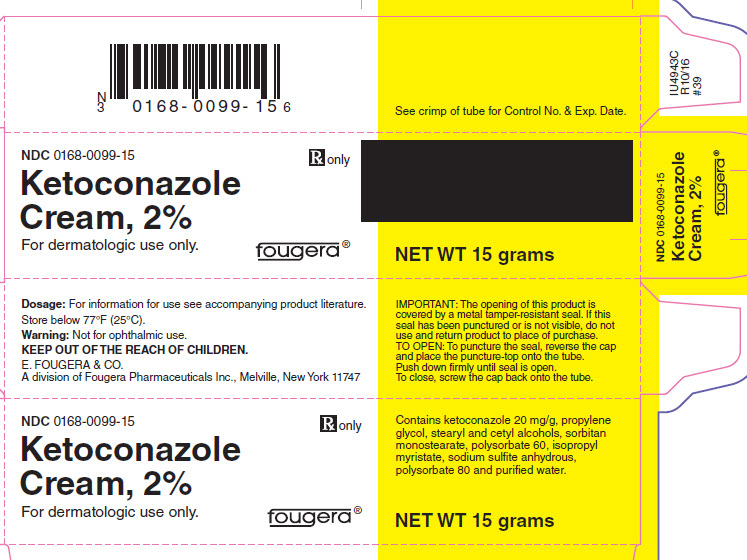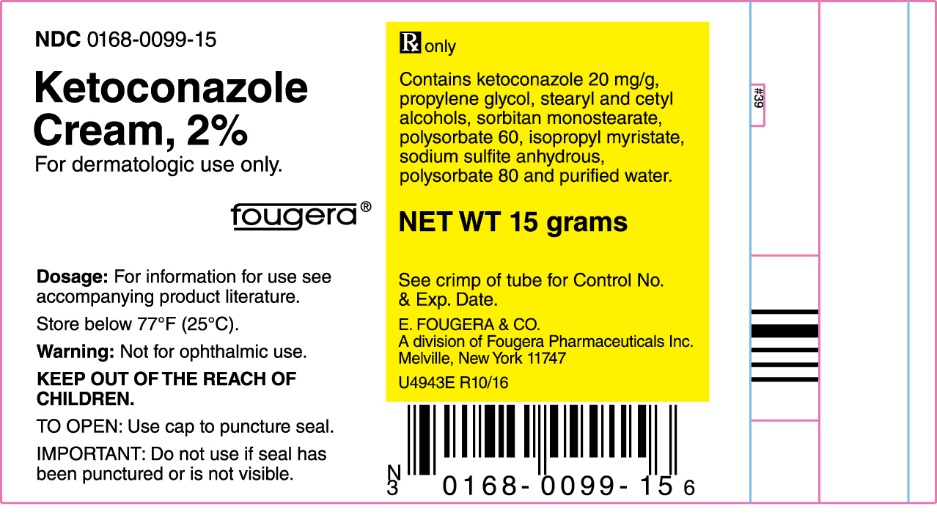 DRUG LABEL: ketoconazole
NDC: 0168-0099 | Form: CREAM
Manufacturer: E. Fougera & Co. a division of Fougera Pharmaceuticals, LLC
Category: prescription | Type: HUMAN PRESCRIPTION DRUG LABEL
Date: 20260128

ACTIVE INGREDIENTS: ketoconazole 20 mg/1 g
INACTIVE INGREDIENTS: propylene glycol; stearyl alcohol; cetyl alcohol; sorbitan monostearate; polysorbate 60; isopropyl myristate; sodium sulfite; polysorbate 80; water

KETOCONAZOLE CREAM 2%

Rx only

DESCRIPTION

Ketoconazole Cream 2%, for topical administration only, contains the broad-spectrum synthetic antifungal agent, ketoconazole 2%, formulated in an aqueous cream vehicle consisting of propylene glycol, stearyl and cetyl alcohols, sorbitan monostearate, polysorbate 60, isopropyl myristate, sodium sulfite anhydrous, polysorbate 80 and purified water.

Ketoconazole is cis-1-acetyl-4-[4-[[2-(2,4-dichlorophenyl)-2-(1H-imidazol-1-ylmethyl)-1,3-dioxolan-4-yl]methoxy]phenyl]piperazine and has the following structural formula:

CLINICAL PHARMACOLOGY

When Ketoconazole Cream 2% was applied dermally to intact or abraded skin of Beagle dogs for 28 consecutive days at a dose of 80 mg, there were no detectable plasma levels using an assay method having a lower detection limit of 2 ng/ml.

After a single topical application to the chest, back and arms of normal volunteers, systemic absorption of ketoconazole was not detected at the 5 ng/ml level in blood over a 72-hour period.

Two dermal irritancy studies, a human sensitization test, a phototoxicity study and a photoallergy study conducted in 38 male and 62 female volunteers showed no contact sensitization of the delayed hypersensitivity type, no irritation, no phototoxicity and no photoallergenic potential due to Ketoconazole Cream 2%.

MICROBIOLOGY

Microbiology: Ketoconazole is a broad spectrum synthetic antifungal agent which inhibits the in vitro growth of the following common dermatophytes and yeasts by altering the permeability of the cell membrane: dermatophytes: Trichophyton rubrum, T. mentagrophytes, T. tonsurans, Microsporum canis, M. audouini, M. gypseum and Epidermophyton floccosum; yeasts: Candida albicans, Malassezia ovale (Pityrosporum ovale) and C. tropicalis; and the organism responsible for tinea versicolor, Malassezia furfur (Pityrosporum orbiculare). Only those organisms listed in the INDICATIONS AND USAGE Section have been proven to be clinically affected. Development of resistance to ketoconazole has not been reported.

Mode of Action: In vitro studies suggest that ketoconazole impairs the synthesis of ergosterol, which is a vital component of fungal cell membranes. It is postulated that the therapeutic effect of ketoconazole in seborrheic dermatitis is due to the reduction of M. ovale, but this has not yet been proven.

INDICATIONS AND USAGE

Ketoconazole Cream 2% is indicated for the topical treatment of tinea corporis, tinea cruris and tinea pedis caused by Trichophyton rubrum, T. mentagrophytes and Epidermophyton floccosum; in the treatment of tinea (pityriasis) versicolor caused by Malassezia furfur (Pityrosporum orbiculare); in the treatment of cutaneous candidiasis caused by Candida spp. and in the treatment of seborrheic dermatitis.

CONTRAINDICATIONS

Ketoconazole Cream 2% is contraindicated in persons who have shown hypersensitivity to the active or excipient ingredients of this formulation.

WARNINGS

Ketoconazole Cream 2% is not for ophthalmic use.

Ketoconazole Cream 2% contains sodium sulfite anhydrous, a sulfite that may cause allergic-type reactions including anaphylactic symptoms and life-threatening or less severe asthmatic episodes in certain susceptible people. The overall prevalence of sulfite sensitivity in the general population is unknown and probably low. Sulfite sensitivity is seen more frequently in asthmatic than in nonasthmatic people.

PRECAUTIONS

GENERAL PRECAUTIONS

General: If a reaction suggesting sensitivity or chemical irritation should occur, use of the medication should be discontinued. Hepatitis (1:10,000 reported incidence) and, at high doses, lowered testosterone and ACTH induced corticosteroid serum levels have been seen with orally administered ketoconazole; these effects have not been seen with topical ketoconazole.

CARCINOGENESIS AND MUTAGENESIS AND IMPAIRMENT OF FERTILITY

Carcinogenesis, Mutagenesis, Impairment of Fertility: A long-term feeding study in Swiss Albino mice and in Wistar rats showed no evidence of oncogenic activity. The dominant lethal mutation test in male and female mice revealed that single oral doses of ketoconazole as high as 80 mg/kg produced no mutation in any stage of germ cell development. The Ames'Salmonella microsomal activator assay was also negative.

Pregnancy: Teratogenic effects: Pregnancy Category C:

Ketoconazole has been shown to be teratogenic (syndactylia and oligodactylia) in the rat when given orally in the diet at 80 mg/kg/day, (10 times the maximum recommended human oral dose). However, these effects may be related to maternal toxicity, which was seen at this and higher dose levels.

There are no adequate and well-controlled studies in pregnant women. Ketoconazole should be used during pregnancy only if the potential benefit justifies the potential risk to the fetus.

NURSING MOTHERS

Nursing Mothers: It is not known whether Ketoconazole Cream 2% administered topically could result in sufficient systemic absorption to produce detectable quantities in breast milk. Nevertheless, a decision should be made whether to discontinue nursing or discontinue the drug, taking into account the importance of the drug to the mother.

PEDIATRIC USE

Pediatric Use: Safety and effectiveness in children have not been established.

ADVERSE REACTIONS

During clinical trials 45 (5.0%) of 905 patients treated with Ketoconazole Cream 2% and 5 (2.4%) of 208 patients treated with placebo reported side effects consisting mainly of severe irritation, pruritus and stinging. One of the patients treated with Ketoconazole Cream developed a painful allergic reaction.

In worldwide postmarketing experience, rare reports of contact dermatitis have been associated with Ketoconazole Cream or one of its excipients, namely sodium sulfite or propylene glycol.

DOSAGE AND ADMINISTRATION

Cutaneous candidiasis, tinea corporis, tinea cruris, tinea pedis and tinea (pityriasis) versicolor: It is recommended that Ketoconazole Cream 2% be applied once daily to cover the affected and immediate surrounding area. Clinical improvement may be seen fairly soon after treatment is begun; however, candidal infections and tinea cruris and corporis should be treated for two weeks in order to reduce the possibility of recurrence. Patients with tinea versicolor usually require two weeks of treatment. Patients with tinea pedis require six weeks of treatment. Seborrheic dermatitis: Ketoconazole Cream 2% should be applied to the affected area twice daily for four weeks or until clinical clearing.

If a patient shows no clinical improvement after the treatment period, the diagnosis should be redetermined.

HOW SUPPLIED

Ketoconazole Cream 2% is supplied as follows:

15 gram NDC 0168-0099-15
30 gram NDC 0168-0099-30
60 gram NDC 0168-0099-60
Store below 77°F (25°C).

E. FOUGERA & CO.
A division of
Fougera
PHARMACEUTICALS INC.
Melville, New York 11747

I299C
R11/11
#39

PACKAGE LABEL – PRINCIPAL DISPLAY PANEL – 15 G CONTAINER

NDC 0168-0099-15

FOUGERA®

KETOCONAZOLE

CREAM 2%

For dermatologic use only.

Rx only

Contains ketoconazole 20 mg/g,

propylene glycol, stearyl and cetyl

alcohols, sorbitan monostearate,

polysorbate 60, isopropyl myristate,

sodium sulfite anhydrous,

polysorbate 80 and purified water.

NET WT 15 grams

PACKAGE LABEL – PRINCIPAL DISPLAY PANEL – 15 G CARTON

NDC 0168-0099-15

Rx only

FOUGERA®

KETOCONAZOLE

CREAM 2%

For dermatologic use only.

Warning: Not for ophthalmic use.

Keep out of reach of children.

NET WT 15 grams